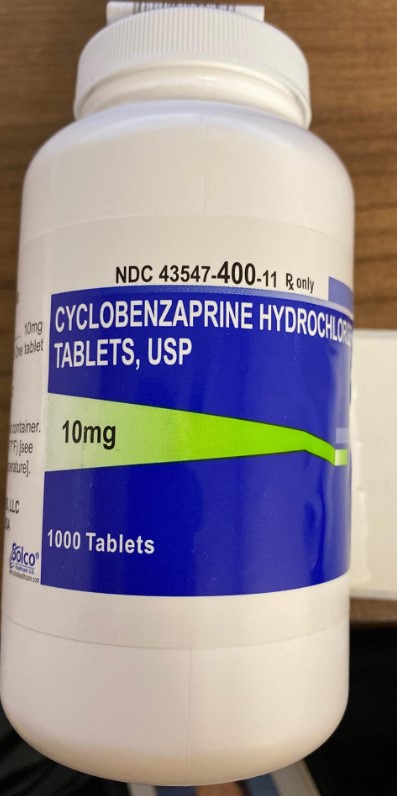 DRUG LABEL: Cyclobenzaprine Hydrochloride
NDC: 80175-0400 | Form: TABLET, FILM COATED
Manufacturer: Central Packaging
Category: prescription | Type: HUMAN PRESCRIPTION DRUG LABEL
Date: 20210219

ACTIVE INGREDIENTS: CYCLOBENZAPRINE HYDROCHLORIDE 10 mg/1 1

INDICATIONS AND USAGE

Cyclobenzaprine hydrochloride tablets are indicated as an adjunct to rest and physical therapy for relief of muscle spasm associated with acute, painful musculoskeletal conditions.

Improvement is manifested by relief of muscle spasm and its associated signs and symptoms, namely, pain, tenderness, limitation of motion, and restriction in activities of daily living.

Cyclobenzaprine hydrochloride tablets should be used only for short periods (up to two or three weeks) because adequate evidence of effectiveness for more prolonged use is not available and because muscle spasm associated with acute, painful musculoskeletal conditions is generally of short duration and specific therapy for longer periods is seldom warranted.

Cyclobenzaprine hydrochloride tablets have not been found effective in the treatment of spasticity associated with cerebral or spinal cord disease, or in children with cerebral palsy.